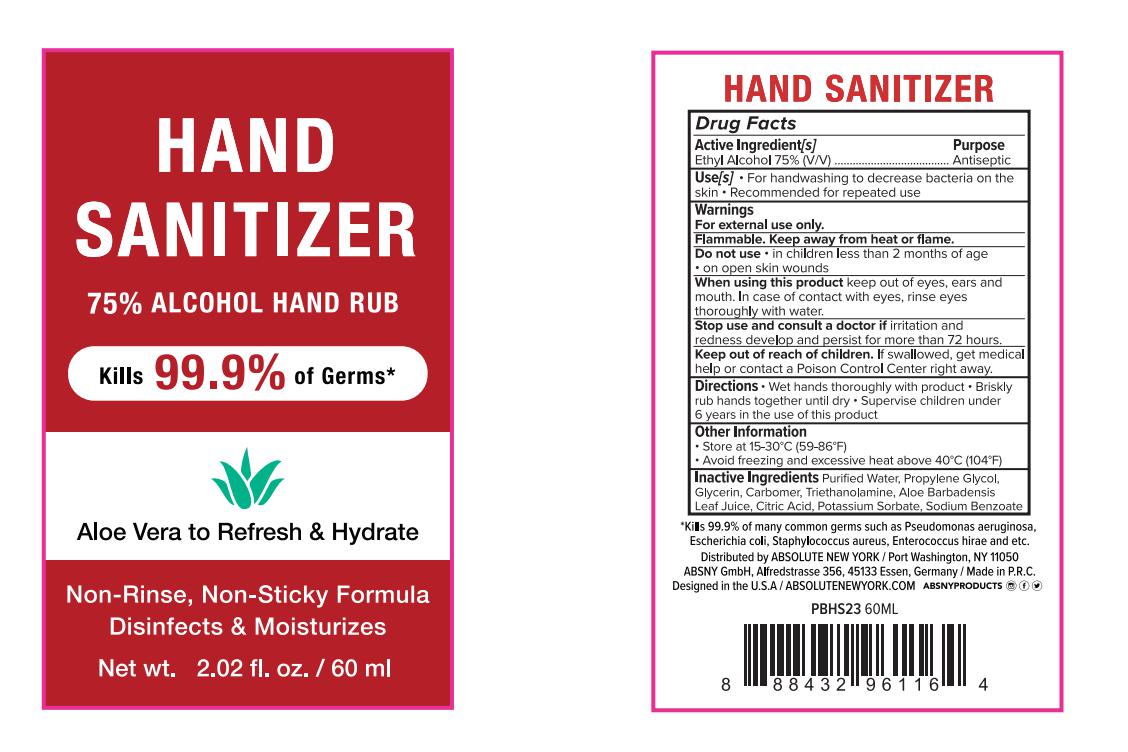 DRUG LABEL: Hand Sanitizer
NDC: 74765-013 | Form: GEL
Manufacturer: Zhejiang Yiwu Limei Cosmetics Co., Ltd
Category: otc | Type: HUMAN OTC DRUG LABEL
Date: 20200530

ACTIVE INGREDIENTS: ALCOHOL 75 mL/100 mL
INACTIVE INGREDIENTS: PROPYLENE GLYCOL; GLYCERIN; TROLAMINE; WATER; CARBOMER 980; ALOE VERA LEAF; ANHYDROUS CITRIC ACID; POTASSIUM SORBATE; SODIUM BENZOATE

NA

Active Ingredient(s)

Ethyl Alcohol 75% v/v. Purpose: Antiseptic

Purpose

Antiseptic, Hand Sanitizer

Use

For handwashing to decrease bacteria on the skin. Recommended for repeated use.

Warnings

For external use only. Flammable. Keep away from heat or flame

Do not use

- in children less than 2 months of age
- on open skin wounds

When using this product keep out of eyes, ears, and mouth. In case of contact with eyes, rinse eyes thoroughly with water.
Stop use and ask a doctor if irritation and redness develop and persist for more than 72 hours.
Keep out of reach of children. If swallowed, get medical help or contact a Poison Control Center right away.

Stop use and ask a doctor if irritation or rash occurs. These may be signs of a serious condition.

Keep out of reach of children. If swallowed, get medical help or contact a Poison Control Center right away.

Directions

- wet hands thoroughly with product.
- Briskly rub hands together until dry.
- supervise children under 6 years in the use of this product

Other information

- Store between 15-30C (59-86F)
- Avoid freezing and excessive heat above 40C (104F)

Inactive ingredients

purified water, propylene glycol , glycerin, carbomer, triethanolamine, aloe barbadensis leaf juice, citric acid, potassium sorbate, sodium benzoate.

Package Label - Principal Display Panel

60 mL NDC: 74765-013-01

300 mL NDC: 74765-013-02

500 mL NDC: 74765-013-03